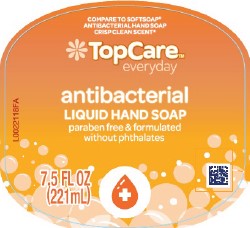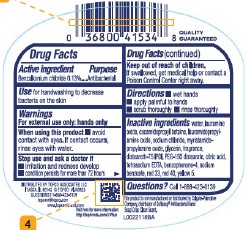 DRUG LABEL: ANTIBACTERIAL
NDC: 76162-279 | Form: LIQUID
Manufacturer: Topco Associates LLC
Category: otc | Type: HUMAN OTC DRUG LABEL
Date: 20260204

ACTIVE INGREDIENTS: BENZALKONIUM CHLORIDE 1.3 mg/1 mL
INACTIVE INGREDIENTS: D&C RED NO. 33; COCAMIDOPROPYL BETAINE; SODIUM CHLORIDE; GLYCERIN; EDETATE SODIUM; SODIUM BENZOATE; WATER; LAURAMINE OXIDE; LAURAMIDOPROPYLAMINE OXIDE; MYRISTAMIDOPROPYLAMINE OXIDE; DISTEARETH-75 IPDI; PEG-150 DISTEARATE; CITRIC ACID; BENZOPHENONE-4; FD&C RED NO. 40; FD&C YELLOW NO. 5

Top Care 279.003/279AD-AE
Light Moisturizing Antibacterial Hand Soap

Active ingredient

Benzalkonium chloride 0.13%

Purpose

Antibacterial

Use

for handwashing to decrease bacteria on the skin

Warnings

For external use only: hands only

When using this product

- avoid contact with eyes. If contact occurs, rinse eyes with water.

Stop use and ask a doctor if

- irritation and redness develop
- condition persists for more than 72 hours

Keep out of reach of children.

If swallowed, get medical help or contact a Poison Control Center right away.

Directions

- wet hands
- apply palmful to hands
- scrub thoroughly
- rinse thoroughly

Inactive ingredients

water, lauramine oxide, cocamidopropyl betaine, lauramidopropylamine oxide, sodium chloride, myristamidopropylamine oxide, glycerin, fragrance, disteareth-75 IPDI, PEG-150 distearate, citric acid, tetrasodium EDTA, benzophenone-4, sodium benzoate, red 33, red 40, yellow 5

Questions?

Call 1-888-423-0139

Adverse Reaction

DISTRIBUTED BY TOPCO ASSOCIATES, LLC

ITASCA, IL 60143 ©TOPCO

QUESTIONS? 1-888-423-0139

topcare@topco.com www.topcarebrands.com

Disclaimer

*This product is not manufactured or distributed by Colgate-Palmolive Company, distributor of Softsoap®Antibacterial Hand Soap Crisp Clean Scent.

Principal Display Panel

COMPARE TO SOFTSOAP®ANTIBACTERIAL HAND SOAP CRISP CLEAN SCENT*

Top Care™

everyday

antibacterial

LIQUID HAND SOAP

paraben free & formulated without phthalates

7.5 FL OZ (221 mL)